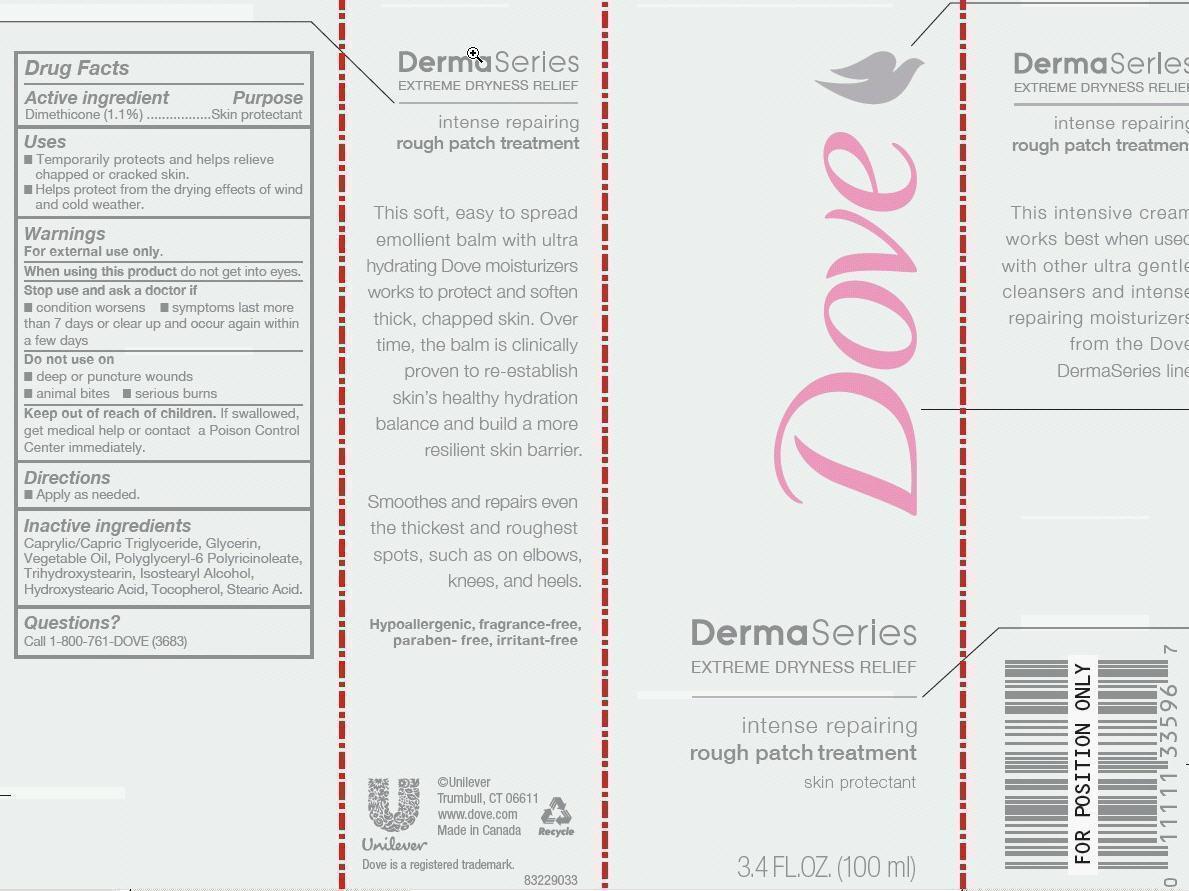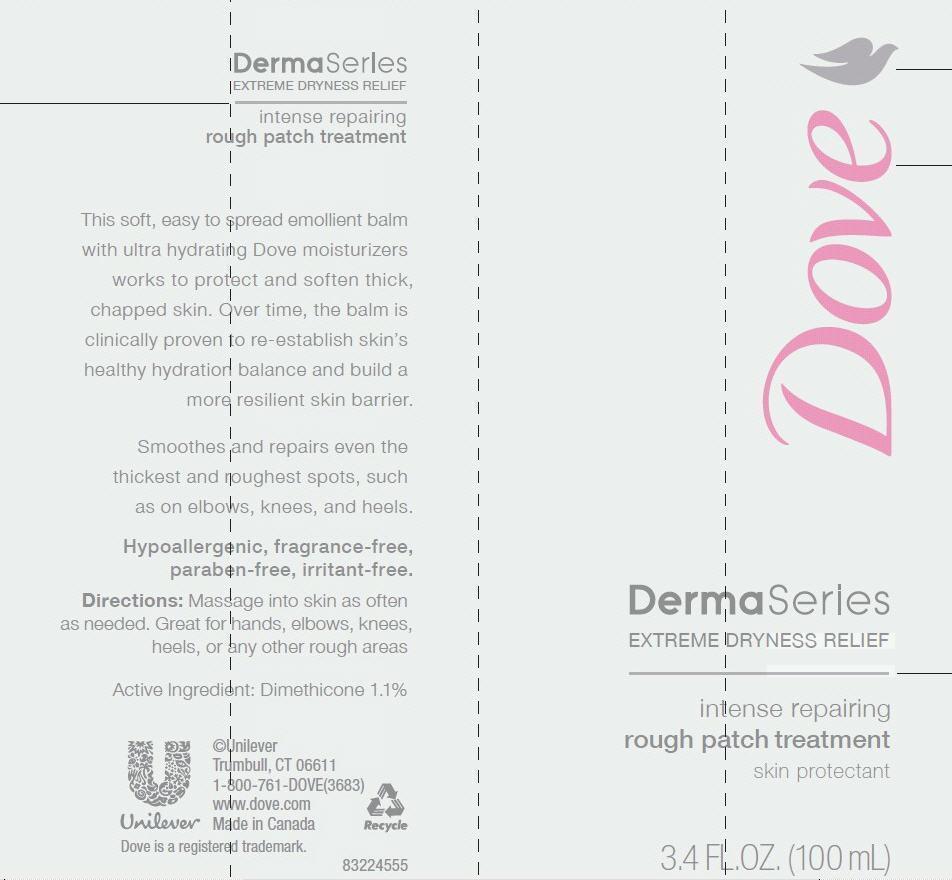 DRUG LABEL: Dove DermaSeries
NDC: 64942-1305 | Form: LOTION
Manufacturer: Conopco Inc. d/b/a Unilever
Category: otc | Type: HUMAN OTC DRUG LABEL
Date: 20221205

ACTIVE INGREDIENTS: DIMETHICONE 1.1 g/100 mL
INACTIVE INGREDIENTS: MEDIUM-CHAIN TRIGLYCERIDES; GLYCERIN; TRIHYDROXYSTEARIN; ISOSTEARYL ALCOHOL; 12-HYDROXYSTEARIC ACID; TOCOPHEROL; STEARIC ACID

Dove DermaSeries Intense Repairing Rough Patch Treatment

Active ingredient

Dimethicone (1.1%)

Purpose

Skin protectant

INDICATIONS AND USAGE

Uses ● temporarily protects and helps relieve chapped or cracked skin ● helps protect from the drying effects of wind and cold weather

WARNINGS
For External Use Only.

When using this product do not get into eyes.

Stop use and ask a doctor if ● condition worsens ● symptoms last more than 7 days or clear up and occur again within a few days.

Do not use on ● deep or puncture wounds ● animal bites ● serious burns

Keep out of reach of children. If swallowed get medical help or contact a Poison Control Center immediately.

Directions

● apply as needed.

Inactive ingredients

Caprylic/Capric Triglyceride, Glycerin, Vegetable Oil, Polyglyceryl-6 Polyricinoleate, Trihydroxystearin, Isostearyl Alcohol, Hydroxstearic Acid, Tocopherol, Stearic Acid.

Questions?

Call 1-800-761-DOVE (3683)